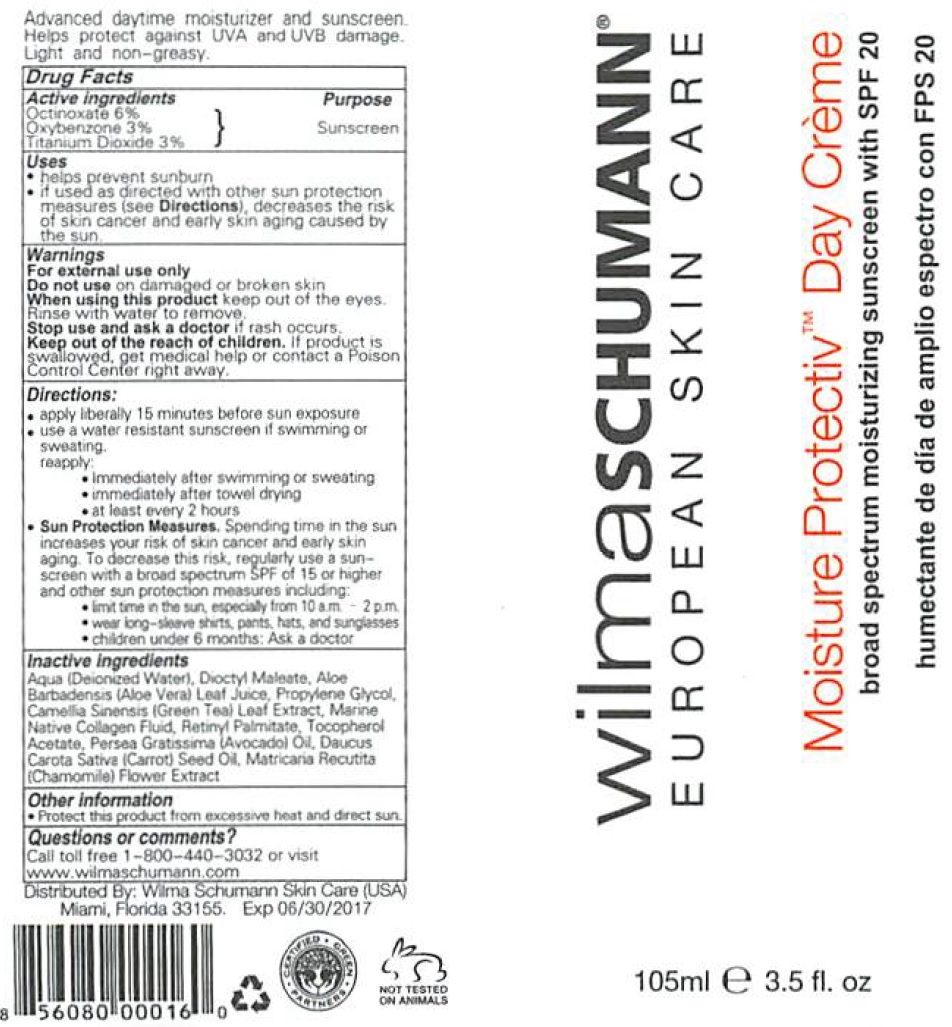 DRUG LABEL: WILMA SCHUMANN Moisture Protektiv Day Cream SPF-20
NDC: 82329-247 | Form: CREAM
Manufacturer: SKINMETICS INC
Category: otc | Type: HUMAN OTC DRUG LABEL
Date: 20231111

ACTIVE INGREDIENTS: OCTINOXATE 60 mg/1 mL; OXYBENZONE 30 mg/1 mL; TITANIUM DIOXIDE 30 mg/1 mL
INACTIVE INGREDIENTS: WATER; DIOCTYL MALEATE; ALOE VERA LEAF; PROPYLENE GLYCOL; GREEN TEA LEAF; VITAMIN A PALMITATE; .ALPHA.-TOCOPHEROL ACETATE; AVOCADO OIL; CARROT SEED OIL; CHAMOMILE

WILMA SCHUMANN Moisture Protektiv Day Cream SPF-20

Active ingredients

Octinoxate 6%

Oxybenzone 3%

Titanium Dioxide 3%

Purpose

Sunscreen

Uses

- helps prevent sunburn
- if used as directed with other sun protection measures (see), decreases the risk of skin cancer and early skin aging caused by the sun. Directions

Warnings

For external use only

Do not ues

on damaged or broken skin

When using this product

keep out of the eyes. Rinse with water to remove.

Stop use and ask a doctor

if rash occurs.

Keep out of reach of children.

If product is swallowed, get medical help or contact a Poison Control Center right away.

Directions:

- apply liberally 15 minutes before sun exposure
- use a water resistant sunscreen if swimming or sweating.

- immediately after swimming or sweating
- immediately after towel drying
- at least every 2 hours
- Spending time in the sun increases your risk of skin cancer and early skin aging. To decrease this risk, regularly use a sunscreen with a broad spectrum SPF of 15 or higher and other sun protection measures including: Sun Protection Measures.
- limit time in the sun, especially from 10 a.m. 0 2 p.m.
- wear long-sleeve shirts, pants, hats, and sunglasses
- children under 6 months: Ask a doctor

reapply:

Inactive ingredients

Aqua (Deionized Water), Dioctyl Maleate, Aloe Barbadensis (Aloe Vera) Leaf Juice, Propylene Glycol, Camellia Sinensis (Green Tea) Leaf Extract, Marine Native Collagen Fluid, Retinyl Palmitate, Tocopherol Acetate, Persea Gratissima (Avocado) Oil, Daucus Carota Sativa (Carrot) Seed Oil, Matricaria Recutita (Chamomile) Flower Extract

Other information

- Protect this product from excessive heat and direct sun.

Questions or comments?

Call toll free 1-800-440-3032 or visit www.wilmaschumann.com